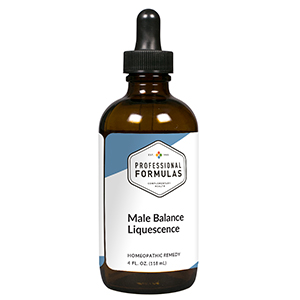 DRUG LABEL: Male Balance Liquescence
NDC: 63083-3034 | Form: LIQUID
Manufacturer: Professional Complementary Health Formulas
Category: homeopathic | Type: HUMAN OTC DRUG LABEL
Date: 20190815

ACTIVE INGREDIENTS: PYGEUM 1 [hp_X]/118 mL; SAW PALMETTO 1 [hp_X]/118 mL; SMILAX ORNATA ROOT 1 [hp_X]/118 mL; ZINC 3 [hp_X]/118 mL; PRASTERONE 4 [hp_X]/118 mL; SUS SCROFA ADRENAL GLAND 6 [hp_X]/118 mL; BOS TAURUS TESTICLE 6 [hp_X]/118 mL; BOS TAURUS PROSTATE GLAND 6 [hp_X]/118 mL; SELENIUM 6 [hp_X]/118 mL; SILVER NITRATE 6 [hp_X]/118 mL; BOS TAURUS PITUITARY GLAND, POSTERIOR 6 [hp_X]/118 mL; BARIUM CARBONATE 12 [hp_X]/118 mL; CHIMAPHILA UMBELLATA WHOLE 12 [hp_X]/118 mL; CONIUM MACULATUM FLOWERING TOP 12 [hp_X]/118 mL; LYCOPODIUM CLAVATUM SPORE 12 [hp_X]/118 mL; GONORRHEAL URETHRAL SECRETION HUMAN 30 [hp_X]/118 mL
INACTIVE INGREDIENTS: ALCOHOL; WATER

T34

ACTIVE INGREDIENTS

Pygeum africanum 1X, 3X, 6X
Sabal serrulata 1X, 3X, 6X
Sarsaparilla 1X, 3X, 6X
Zincum metallicum 3X
DHEA 4X
Adrenal 6X
Orchic 6X
Prostate 6X
Selenium metallicum 6X
Argentum nitricum 6X, 12X
Pituitary 6X, 12X
Baryta carbonica 12X
Chimaphila umbellata 12X
Conium maculatum 12X
Lycopodium clavatum 12X
Medorrhinum 30X

QUESTIONS

Professional Formulas

PO Box 2034 Lake Oswego, OR 97035

INDICATIONS

For the temporary relief of diminished sexual desire or performance, muscle weakness or decreased strength, sleep disturbances, weight gain, or fatigue.*

PURPOSE

*Claims based on traditional homeopathic practice, not accepted medical evidence. Not FDA evaluated.

WARNINGS

Consult a doctor if condition worsens or if symptoms persist. Keep out of the reach of children. In case of overdose, get medical help or contact a poison control center right away. If pregnant or breastfeeding, ask a healthcare professional before use.

Keep out of the reach of children.

PREGNANCY OR BREAST FEEDING

If pregnant or breastfeeding, ask a healthcare professional before use.

DIRECTIONS

Place drops under tongue 30 minutes before/after meals. Adults and children 12 years and over: Take one full dropper up to 2 times per day. Consult a physician for use in children under 12 years of age.

OTHER INFORMATION

Tamper resistant. If seal is broken, do not use. After opening, close container tightly and store at room temperature away from heat.

INACTIVE INGREDIENTS

20% ethanol, purified water.

LABEL

Est 1985

Professional Formulas

Complementary Health

Male Balance Liquescence

Homeopathic Remedy

4 FL. OZ. (118 mL)